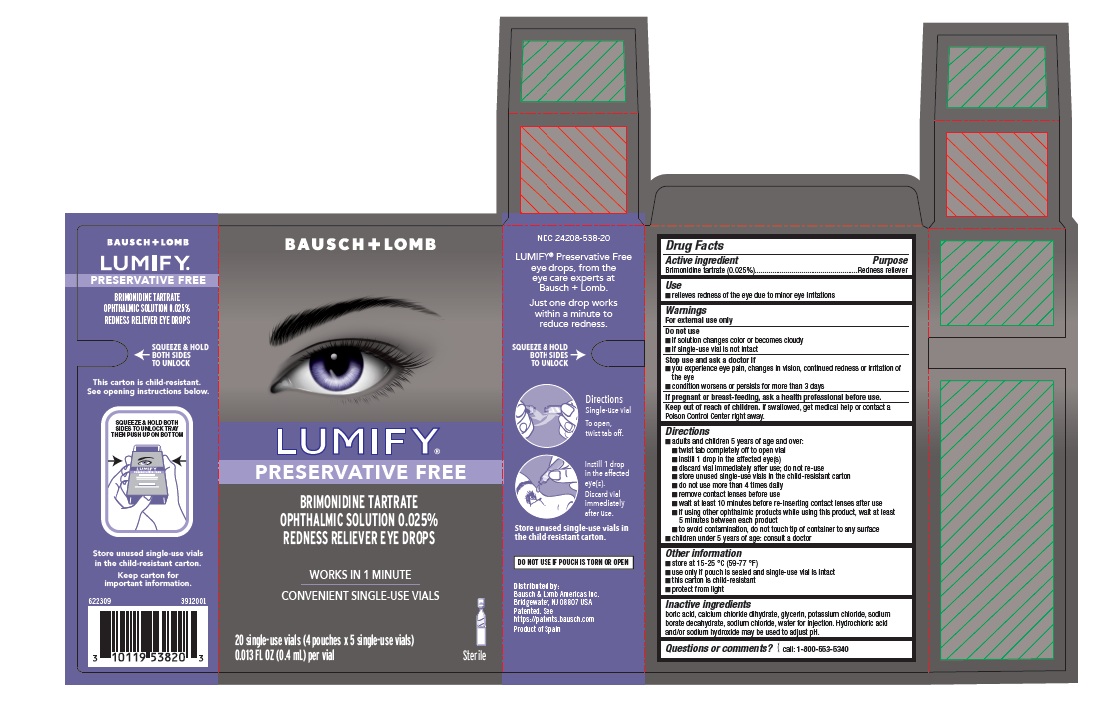 DRUG LABEL: LUMIFY PRESERVATIVE FREE EYE DROPS
NDC: 24208-538 | Form: SOLUTION/ DROPS
Manufacturer: Bausch & Lomb Incorporated
Category: otc | Type: HUMAN OTC DRUG LABEL
Date: 20260207

ACTIVE INGREDIENTS: BRIMONIDINE TARTRATE 0.25 mg/1 mL
INACTIVE INGREDIENTS: BORIC ACID; CALCIUM CHLORIDE; GLYCERIN; POTASSIUM CHLORIDE; SODIUM BORATE; SODIUM CHLORIDE; WATER; SODIUM HYDROXIDE; HYDROCHLORIC ACID

Lumify®Preservative Free

Active ingredient

Brimonidine tartrate (0.025%)

Purpose

Redness reliever

Use

- relieves redness of the eye due to minor eye irritations

Warnings

For external use only

Do not use

- if solution changes color or becomes cloudy
- if single-use vial is not intact

Stop use and ask a doctor if

- you experience eye pain, changes in vision, continued redness or irritation of the eye
- condition worsens or persists for more than 3 days

Keep out of reach of children

If swallowed, get medical help or contact a Poison Control Center right away.

Directions

- adults and children 5 years of age and over:
  - twist tab completely off to open vial
  - instill 1 drop in the affected eye(s)
  - discard vial immediately after use; do not re-use
  - store unused single-use vials in the child-resistant carton
  - do not use more than 4 times daily
  - remove contact lenses before use
  - wait at least 10 minutes before re-inserting contact lenses after use
  - if using other ophthalmic products while using this product, wait at least 5 minutes between each product
  - to avoid contamination, do not touch tip of container to any surface
- children under 5 years of age: consult a doctor

Other information

- store at 15-25 °C (59-77 °F)
- use only if pouch is sealed and single-use vial is intact
- this carton is child-resistant
- protect from light

Inactive Ingredients

boric acid, calcium chloride dihydrate, glycerin, potassium chloride, sodium borate decahydrate, sodium chloride, water for injection. Hydrochloric acid and/or sodium hydroxide may be used to adjust pH.

Package/Label Principal Display Panel- 20 ct Carton

BAUSCH + LOMB

[Eye Image]

LUMIFY®

PRESERVATIVE FREE

BRIMONIDINE TARTRATE
OPHTHALMIC SOLUTION 0.025%
REDNESS RELIEVER EYE DROPS

WORKS IN 1 MINUTE

CONVENIENT SINGLE-USE VIALS

20 single-use vials (4 pouches x 5 single-use vials)

0.013 FL OZ (0.4 mL) per vial

[vial icon]
Sterile

622309
3912001